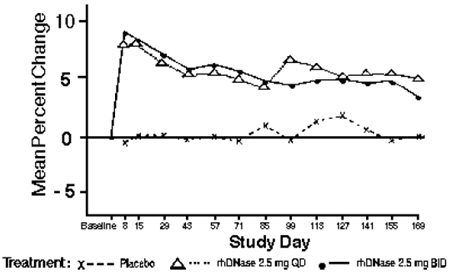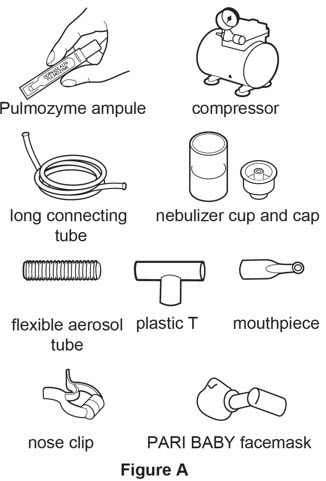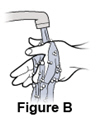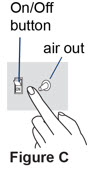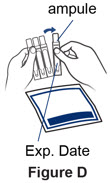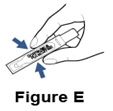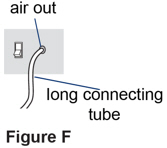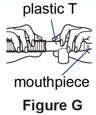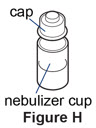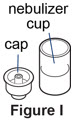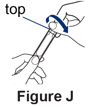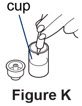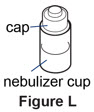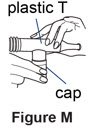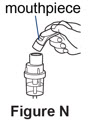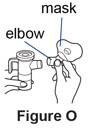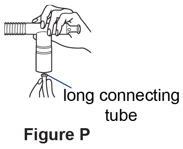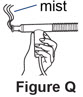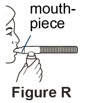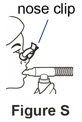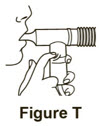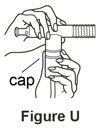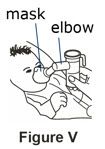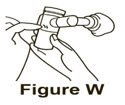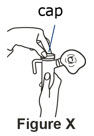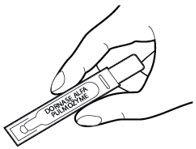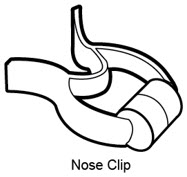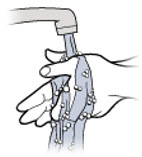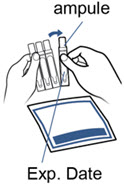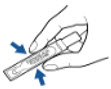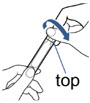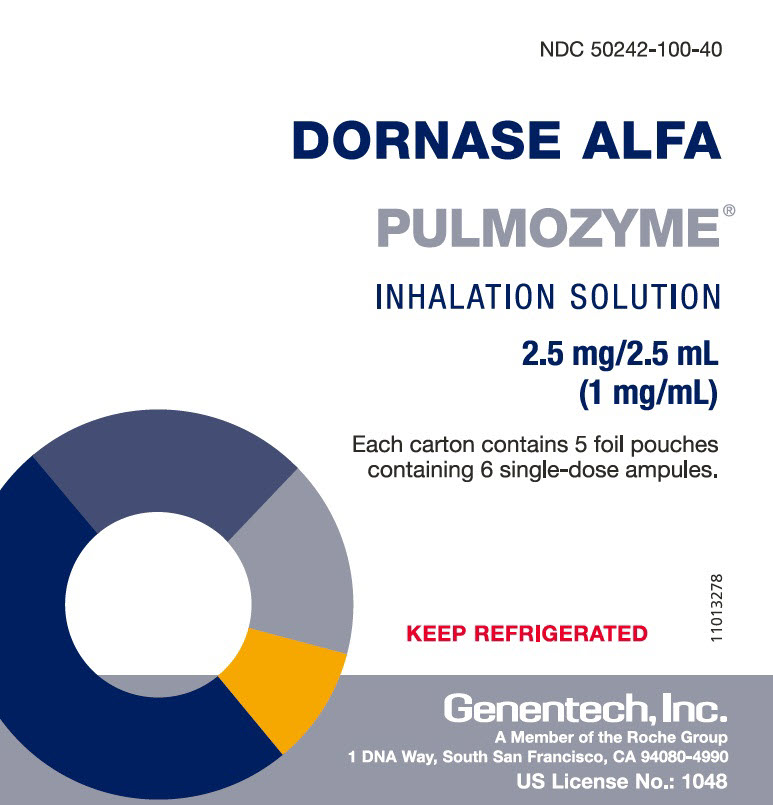 DRUG LABEL: Pulmozyme
NDC: 50242-100 | Form: SOLUTION
Manufacturer: Genentech, Inc.
Category: prescription | Type: HUMAN PRESCRIPTION DRUG LABEL
Date: 20251217

ACTIVE INGREDIENTS: DORNASE ALFA 1 mg/1 mL
INACTIVE INGREDIENTS: CALCIUM CHLORIDE 0.15 mg/1 mL; SODIUM CHLORIDE 8.77 mg/1 mL

HIGHLIGHTS OF PRESCRIBING INFORMATION

These highlights do not include all the information needed to use PULMOZYME safely and effectively. See full prescribing information for PULMOZYME.
PULMOZYME® (dornase alfa) inhalation solution, for inhalation use
Initial U.S. Approval: 1993

RECENT MAJOR CHANGES

Dosage and Administration. (2.1, 2.2) | 02/2024

1 INDICATIONS AND USAGE

PULMOZYME is a recombinant DNase enzyme indicated in conjunction with standard therapies for the management of cystic fibrosis (CF) patients to improve pulmonary function. (1)

2 DOSAGE AND ADMINISTRATION

- The recommended dosage is 2.5 mg (one single-dose ampule) inhaled once daily using a recommended nebulizer. (2.1)
- Some patients may benefit from twice daily administration. (2.1)
- See full prescribing information for the recommended nebulizers for use with PULMOZYME. (2.2)

3 DOSAGE FORMS AND STRENGTHS

Inhalation solution: 2.5 mg/2.5 mL (1 mg/mL) clear, colorless solution in single-dose ampules (3)

4 CONTRAINDICATIONS

PULMOZYME is contraindicated in patients with known hypersensitivity to dornase alfa, Chinese Hamster Ovary cell products, or any component of the product. (4)

5 WARNINGS AND PRECAUTIONS

None. (5)

6 ADVERSE REACTIONS

The most common adverse reactions (occurring in ≥3% of patients treated with PULMOZYME over placebo) seen in clinical trials in CF patients were: voice alteration, pharyngitis, rash, laryngitis, chest pain, conjunctivitis, rhinitis, decrease in FVC of ≥10%, fever, and dyspnea. (6.1)

To report SUSPECTED ADVERSE REACTIONS, contact Genentech at 1-888-835-2555 or FDA at 1-800-FDA-1088 or www.fda.gov/medwatch.

FULL PRESCRIBING INFORMATION

1 INDICATIONS AND USAGE

PULMOZYME® is indicated, in conjunction with standard therapies, for the management of pediatric and adult patients with cystic fibrosis (CF) to improve pulmonary function.

In CF patients with an FVC ≥ 40% of predicted, daily administration of PULMOZYME has also been shown to reduce the risk of respiratory tract infections requiring parenteral antibiotics.

2 DOSAGE AND ADMINISTRATION

2.1 Recommended Dosage

The recommended dosage, in most cystic fibrosis patients, is 2.5 mg (one single-dose ampule) inhaled once daily using a recommended jet nebulizer connected to an air compressor system or via a vibrating mesh nebulizer [see Dosage and Administration (2.2)].

Some patients may benefit from twice daily administration [see Clinical Studies (14)].

2.2 Administration Instructions

Nebulizer Information

- Administer PULMOZYME via a jet nebulizer connected to an air compressor with an adequate air flow and equipped with a mouthpiece or suitable face mask, or via a vibrating mesh nebulizer. Refer to Table 1 for the recommended Jet Nebulizers or Vibrating Mesh Nebulizers for use with PULMOZYME. No data are currently available to support the administration of PULMOZYME with other nebulizer systems.
- The eRapid Nebulizer System should only be used by adults and pediatric patients who can use a mouthpiece, and not by younger patients who need a mask to inhale PULMOZYME.
- Use the selected nebulizer in accordance with the manufacturer's instruction manual.
- Refer to the manufacturer's instruction manual on the use, maintenance, and replacement of the equipment, including cleaning and disinfection procedures for the selected nebulizer.
- For additional information, refer to the selected nebulizer manufacturer's instruction manual.

Table 1. Recommended Jet Nebulizers or Vibrating Mesh Nebulizers for Use with PULMOZYME
Jet Nebulizer [Follow the selected nebulizer manufacturer's instruction manual.] | Compressor
Hudson T Up-draft II® | Pulmo-Aide® or legally marketed compressor of identical pressure and flow rate (maximum 30 psi, 12 LPM).
Marquest Acorn II® | Pulmo-Aide® or legally marketed compressor of identical pressure and flow rate (maximum 30 psi, 12 LPM).
PARI LC® Plus | PARI PRONEB® or legally marketed compressor of identical pressure and flow rate (maximum 24 psi, 9 LPM).
PARI BABY™ [Patients who are unable to inhale or exhale orally throughout the entire nebulization period may use the PARI BABY™ nebulizer.] | PARI PRONEB® or legally marketed compressor of identical pressure and flow rate (maximum 24 psi, 9 LPM).
Durable Sidestream® | MOBILAIRE™, Porta-NEB® or legally marketed compressor of identical pressure and flow rate (maximum 45 psi, 7 LPM).
Vibrating Mesh Nebulizers
eRapid® Nebulizer System [Consisting of the eRapid® Nebulizer Handset with eBase™ Controller. Avoid use in patients who need a mask to inhale PULMOZYME.]
Innospire Go
Pulmogine Vibrating Mesh Nebulizer
AireHealth Nebulizer™
Intelligent Mesh Nebulizer

PULMOZYME Information

- Each PULMOZYME ampule should be squeezed prior to use in order to check for leaks. Discard ampules if the solution is cloudy or discolored. Once opened, the entire contents of the ampule must be used or discarded.
- Do not dilute or mix PULMOZYME with other drugs in the nebulizer. Mixing of PULMOZYME with other drugs could lead to adverse physicochemical and/or functional changes in PULMOZYME or the admixed compound.

3 DOSAGE FORMS AND STRENGTHS

Inhalation solution: 2.5 mg/2.5 mL (1 mg/mL) clear, colorless solution in single-dose ampules.

4 CONTRAINDICATIONS

PULMOZYME is contraindicated in patients with known hypersensitivity to dornase alfa, Chinese Hamster Ovary cell products, or any component of the product.

5 WARNINGS AND PRECAUTIONS

None.

6 ADVERSE REACTIONS

6.1 Clinical Trials Experience

Because clinical trials are conducted under widely varying conditions, adverse reaction rates observed in the clinical trials of a drug cannot be directly compared to rates in the clinical trials of another drug and may not reflect the rates observed in practice.

The data described below reflect exposure to PULMOZYME in 902 patients, with exposures ranging from 2 weeks of daily administration up to once or twice daily administration for six months. PULMOZYME was studied in both placebo-controlled (n=804) and uncontrolled trials (n=98). The population of patients in placebo-controlled trials was with FVC ≥ 40% of predicted (n=643) or with more advanced pulmonary disease, FVC < 40% of predicted (n=161). The population in the uncontrolled trial included 98 pediatric patients with CF ranging from 3 months to 10 years of age. More than half of the patients received PULMOZYME 2.5 mg by inhalation once a day (n=581), while the rest of patients (n=321) received PULMOZYME 2.5 mg by inhalation twice a day.

Placebo-Controlled Trials

Trial 1: Trial 1 was a randomized, placebo-controlled clinical trial in patients with FVC ≥ 40% of predicted. In this trial, over 600 patients received PULMOZYME once or twice daily for six months. The most common adverse reaction (risk difference ≥5%) was voice alteration. The proportion of most adverse events was similar for patients on PULMOZYME and on placebo, probably reflecting the sequelae of the underlying lung disease. In most cases reactions that were increased were mild, transient in nature, and did not require alterations in dosing. Few patients experienced adverse reactions resulting in permanent discontinuation from PULMOZYME, and the proportion of discontinuations were similar for placebo (2%) and PULMOZYME (3%). Adverse reactions occurring in a higher proportion (greater than 3%) of PULMOZYME treated patients than in placebo-treated patients are listed in Table 2.

Trial 2: Trial 2 was a randomized, placebo-controlled trial in patients with more advanced pulmonary disease (FVC < 40% of predicted) who were treated for 12 weeks. In this trial, the safety profile of PULMOZYME was similar to that reported in patients with less advanced pulmonary disease (FVC ≥ 40% of predicted). Adverse reactions that were reported in this trial with a higher proportion (greater than 3%) in the PULMOZYME treated patients are listed in Table 2.

Table 2. Adverse Reactions Increased 3% or More in PULMOZYME Treated Patients Over Placebo in CF Clinical Trials
Adverse Reactions (of any severity or seriousness) | Trial 1 CF Patients with FVC ≥ 40% of predicted treated for 24 weeks |  |  | Trial 2 CF Patients with FVC <40% of predicted treated for 12 weeks
Adverse Reactions (of any severity or seriousness) | Placebo n=325 | Pulmozyme QD n=322 | Pulmozyme BID n=321 | Placebo n=159 | Pulmozyme QD n=161
Voice alteration | 7% | 12% | 16% | 6% | 18%
Pharyngitis | 33% | 36% | 40% | 28% | 32%
Rash | 7% | 10% | 12% | 1% | 3%
Laryngitis | 1% | 3% | 4% | 1% | 3%
Chest Pain | 16% | 18% | 21% | 23% | 25%
Conjunctivitis | 2% | 4% | 5% | 0% | 1%
Rhinitis | Differences were less than 3% |  |  | 24% | 30%
FVC decrease of ≥ 10% of predicted [Single measurement only, does not reflect overall FVC changes.] | Differences were less than 3% |  |  | 17% | 22%
Fever | Differences were less than 3% |  |  | 28% | 32%
Dyspepsia | Differences were less than 3% |  |  | 0% | 3%
Dyspnea (when reported as serious) | Differences were less than 3% |  |  | 12% [Total reports of dyspnea (regardless of severity or seriousness) had a difference of less than 3% in Trial 2.] | 17%

Mortality rates observed in controlled trials were similar for the placebo and PULMOZYME treated patients. Causes of death were consistent with progression of cystic fibrosis and included apnea, cardiac arrest, cardiopulmonary arrest, cor pulmonale, heart failure, massive hemoptysis, pneumonia, pneumothorax, and respiratory failure.

Uncontrolled Trial

Trial 3: The safety of PULMOZYME, 2.5 mg by inhalation, was studied with 2 weeks of daily administration in 98 pediatric patients with cystic fibrosis 3 months to 10 years of age (65 aged 3 months to < 5 years, 33 aged 5 to ≤ 10 years). The PARI BABY™ reusable nebulizer (which uses a facemask instead of a mouthpiece) was utilized in patients unable to demonstrate the ability to inhale or exhale orally throughout the entire treatment period (54/65, 83% of the younger and 2/33, 6% of the older patients). Overall, the nature of adverse reactions was similar to that seen in the placebo-controlled trials. The number of patients reporting cough was higher in the younger age group as compared to the older age group (29/65, 45% compared to 10/33, 30%) as was the number reporting moderate to severe cough (24/65, 37% as compared to 6/33, 18%). The number of patients reporting rhinitis was higher in the younger age group as compared to the older age group (23/65, 35% compared to 9/33, 27%) as was the number reporting rash (4/65, 6% as compared to 0/33).

Allergic Reactions

There have been no reports of anaphylaxis attributed to the administration of PULMOZYME. Urticaria, mild to moderate, and mild skin rash have been observed and have been transient. Within all of the studies, a small percentage (average of 2-4%) of patients treated with PULMOZYME developed serum antibodies to PULMOZYME. None of these patients developed anaphylaxis, and the clinical significance of serum antibodies to PULMOZYME is unknown.

7 DRUG INTERACTIONS

Available data indicate there are no clinically important drug-drug interactions with PULMOZYME.

8 USE IN SPECIFIC POPULATIONS

8.1 Pregnancy

TERATOGENIC EFFECTS

Risk Summary

There are no adequate and well-controlled studies with PULMOZYME in pregnant women. However, animal reproduction studies have been conducted with dornase alfa. In these studies, no evidence of fetal harm was observed in rats and rabbits at doses of dornase alfa up to approximately 600 times the maximum recommended human dose (MRHD).

The background risk of major birth defects and miscarriage for the cystic fibrosis population is unknown. However, the background risk in the U.S. general population of major birth defects is 2-4% and of miscarriage is 15-20% of clinically recognized pregnancies.

Data

Animal Data

Reproductive studies have been performed in rats and rabbits at intravenous doses of dornase alfa up to 10 mg/kg/day (approximately 600 times the MRHD in adults). In a combined embryo-fetal development and pre- and post-natal development study, no evidence of maternal toxicity, embryotoxicity, or teratogenicity was observed when dornase alfa was administered to dams throughout organogenesis (Gestation days 6 to 17). Dornase alfa did not elicit adverse effects on fetal or neonatal growth when administered to dams throughout most of gestation and delivery (Gestation days 6 to 25) and nursing (Post-partum days 6 to 21).

A pharmacokinetic study in Cynomolgus monkeys found no detectable levels of dornase alfa in fetal blood or amniotic fluid on gestation day 150 (end of gestation) from mothers that were administered an intravenous bolus dose (0.1 mg/kg) followed by an intravenous infusion dose (0.080 mg/kg) over a 6-hour period during pregnancy.

8.2 Lactation

Risk Summary

It is not known whether PULMOZYME is present in human milk. In a pharmacokinetic study in Cynomolgus monkeys, levels of dornase alfa detected in milk were less than 0.1% of the maternal serum concentration at 24 hours after dosing [intravenous bolus dose (0.1 mg/kg) of dornase alfa followed by an intravenous infusion (0.080 mg/kg/hr) over a 6-hour period] on post-partum day 14. The developmental and health benefits of breastfeeding should be considered along with the mother's clinical need for PULMOZYME and any potential adverse effects on the breastfed child from PULMOZYME or from the underlying maternal condition.

8.4 Pediatric Use

The safety and effectiveness of PULMOZYME in conjunction with standard therapies for cystic fibrosis have been established in pediatric patients. Use of PULMOZYME in pediatric patients is supported by evidence in the following age groups:

- Patients 5 to 17 years of age: Use of PULMOZYME in patients 5 to 17 years of age is supported by evidence from a randomized, placebo-controlled trial of 303 of clinically stable cystic fibrosis patients 5 to 17 years of age who received PULMOZYME [see Clinical Studies (14)].
- Patients less than 5 years: Use of PULMOZYME in patients less than 5 years of age is supported by extrapolation of efficacy data in patients 5 years of age and older with additional safety data in 65 pediatric patients aged 3 months to less than 5 years who received PULMOZYME 2.5 mg daily by inhalation for 2 weeks [see Adverse Reactions (6.1) and Clinical Studies (14)].

8.5 Geriatric Use

Cystic fibrosis is primarily a disease of children and young adults. Clinical studies of PULMOZYME did not include sufficient numbers of subjects aged 65 or older to determine whether they respond differently from younger subjects.

11 DESCRIPTION

Dornase alfa is a recombinant human deoxyribonuclease I (rhDNase) an enzyme which selectively cleaves DNA. The protein is produced by genetically engineered Chinese Hamster Ovary (CHO) cells containing DNA encoding for the native human protein, deoxyribonuclease I (DNase). The product is purified by column chromatography and tangential flow filtration. The purified glycoprotein contains 260 amino acids with an approximate molecular weight of 37,000 daltons. The primary amino acid sequence is identical to that of the native human enzyme.

PULMOZYME (dornase alfa) inhalation solution is administered by inhalation of an aerosol mist produced by a compressed air driven nebulizer or a recommended nebulizer system [see Clinical Studies (14) and Dosage and Administration (2.2)]. PULMOZYME is a sterile, clear, colorless, highly purified solution in single-dose ampules. Each ampule delivers 2.5 mL of the solution to the nebulizer bowl. Each mL of aqueous solution contains 1 mg dornase alfa, calcium chloride dihydrate (0.15 mg) and sodium chloride (8.77 mg). The solution contains no preservative. The nominal pH of the solution is 6.3.

12 CLINICAL PHARMACOLOGY

12.1 Mechanism of Action

PULMOZYME is recombinant human deoxyribonuclease I (rhDNase), an enzyme which selectively cleaves DNA. In preclinical in vitro studies, PULMOZYME hydrolyzes the DNA in sputum of CF patients and reduces sputum viscoelasticity. In CF patients, retention of viscous purulent secretions in the airways contributes both to reduced pulmonary function and to exacerbations of infection. Purulent pulmonary secretions contain very high concentrations of extracellular DNA released by degenerating leukocytes that accumulate in response to infection.

12.3 Pharmacokinetics

When 2.5 mg PULMOZYME was administered by inhalation to eighteen CF patients, mean sputum concentrations of 3 µg/mL DNase were measurable within 15 minutes. Mean sputum concentrations declined to an average of 0.6 µg/mL two hours following inhalation. Inhalation of up to 10 mg TID of PULMOZYME by 4 CF patients for six consecutive days, did not result in a significant elevation of serum concentrations of DNase above normal endogenous levels. After administration of up to 2.5 mg of PULMOZYME twice daily for six months to 321 CF patients, no accumulation of serum DNase was noted. Dornase alfa is expected to be metabolized by proteases present in biological fluids. A human intravenous dose study suggested an elimination half-life of 3-4 hours for dornase alfa.

PULMOZYME, 2.5 mg by inhalation, was administered daily to 98 patients aged 3 months to ≤ 10 years, and bronchoalveolar lavage (BAL) fluid was obtained within 90 minutes of the first dose. BAL DNase concentrations were detectable in all patients but showed a broad range, from 0.007 to 1.8 µg/mL. Over an average of 14 days of exposure, serum DNase concentrations (mean ± s.d.) increased by 1.1 ± 1.6 ng/mL for the 3 months to < 5 year age group and by 0.8 ± 1.2 ng/mL for the 5 to ≤ 10 year age group. The relationship between BAL or serum DNase concentration and adverse experiences and clinical outcomes is unknown.

13 NONCLINICAL TOXICOLOGY

13.1 Carcinogenesis, Mutagenesis, Impairment of Fertility

PULMOZYME produced no treatment-related increases in the incidence of tumors in a lifetime study in Sprague Dawley rats that were administered inhaled doses up to 0.246 mg/kg/day (approximately 30 times the MRHD in adults). There was no increase in the development of benign or malignant neoplasms and no occurrence of unusual tumor types in rats after lifetime exposure.

PULMOZYME tested negative in the following genotoxicity assays: the in vitro Ames assay, in vitro mouse lymphoma assay, and in vivo mouse bone marrow micronucleus assay. No evidence of impairment of fertility was observed in male and female rats that received intravenous doses up to 10 mg/kg/day (approximately 600 times the MRHD in adults).

14 CLINICAL STUDIES

Trial in CF Patients with FVC ≥40% of Predicted

PULMOZYME has been evaluated in a randomized, placebo-controlled trial of clinically stable cystic fibrosis patients, 5 years of age and older, with baseline forced vital capacity (FVC) greater than or equal to 40% of predicted and receiving standard therapies for cystic fibrosis. Patients were treated with placebo (325 patients), 2.5 mg of PULMOZYME once a day (322 patients), or 2.5 mg of PULMOZYME twice a day (321 patients) for six months administered via a Hudson T Up-draft II® nebulizer with a Pulmo-Aide® compressor.

Both doses of PULMOZYME resulted in significant reductions in the number of patients experiencing respiratory tract infections requiring use of parenteral antibiotics compared with the placebo group. Administration of PULMOZYME reduced the relative risk of developing a respiratory tract infection by 27% and 29% for the 2.5 mg daily dose and the 2.5 mg twice daily dose, respectively (see Table 3). The data suggest that the effects of PULMOZYME on respiratory tract infections in older patients (> 21 years) may be smaller than in younger patients, and that twice daily dosing may be required in the older patients. Patients with baseline FVC > 85% may also benefit from twice a day dosing (see Table 3). The reduced risk of respiratory infection observed in PULMOZYME treated patients did not directly correlate with improvement in FEV1 during the initial two weeks of therapy.

Within 8 days of the start of treatment with PULMOZYME, mean FEV1 increased 7.9% in those treated once a day and 9.0% in those treated twice a day compared to the baseline values. The overall mean FEV1 during long-term therapy increased 5.8% from baseline at the 2.5 mg daily dose level and 5.6% from baseline at the 2.5 mg twice daily dose level. Placebo recipients did not show significant mean changes in pulmonary function testing (see Figure 1).

For patients 5 years of age or older, with baseline FVC greater than or equal to 40%, administration of PULMOZYME decreased the incidence of occurrence of first respiratory tract infection requiring parenteral antibiotics, and improved mean FEV1, regardless of age or baseline FVC.

Table 3. Incidence of First Respiratory Tract Infection Requiring Parenteral Antibiotics in Patients with FVC ≥40% of Predicted
 | Placebo N=325 | 2.5 mg QD N=322 | 2.5 mg BID N=321
Percent of Patients Infected | 43% | 34% | 33%
Relative Risk (vs placebo) |  | 0.73 | 0.71
p-value (vs placebo) |  | 0.015 | 0.007
Subgroup by Age and Baseline FVC | Placebo % (N) | 2.5 mg QD % (N) | 2.5 mg BID % (N)
Age
5-20 years | 42% (201) | 25% (199) | 28% (184)
21 years and older | 44% (124) | 48% (123) | 39% (137)
Baseline FVC
40-85% Predicted | 54% (194) | 41% (201) | 44% (203)
> 85% Predicted | 27% (131) | 21% (121) | 14% (118)

Figure 1. Mean Percent Change from Baseline FEV1 in Patients with FVC ≥40% of Predicted

Trial in CF Patients with FVC <40% of Predicted

PULMOZYME has also been evaluated in a second randomized, placebo-controlled trial in clinically stable patients with baseline FVC < 40% of predicted. Patients were enrolled and treated with placebo (162 patients) or PULMOZYME 2.5 mg QD (158 patients) for twelve weeks. In patients who received PULMOZYME, there was an increase in mean change (as percent of baseline) compared to placebo in FEV1 (9.4% vs. 2.1%, p < 0.001) and in FVC (12.4% vs. 7.3%, p < 0.01). PULMOZYME did not significantly reduce the risk of developing a respiratory tract infection requiring parenteral antibiotics (54% of PULMOZYME patients vs. 55% of placebo patients had experienced a respiratory tract infection by 12 weeks, relative risk = .93, p = 0.62).

The effect of PULMOZYME on exercise tolerance has not been established in adult and pediatric patients.

Other Studies

Clinical trials have indicated that PULMOZYME therapy can be continued or initiated during an acute respiratory exacerbation.

Short-term dose ranging studies demonstrated that doses in excess of 2.5 mg BID did not provide further improvement in FEV1. Patients who have received drug on a cyclical regimen (i.e., administration of PULMOZYME 10 mg BID for 14 days, followed by a 14 day wash out period) showed rapid improvement in FEV1 with the initiation of each cycle and a return to baseline with each PULMOZYME withdrawal.

16 HOW SUPPLIED/STORAGE AND HANDLING

PULMOZYME (dornase alfa) inhalation solution is a sterile, clear, colorless solution supplied in:

- 30 unit cartons containing 5 foil pouches of 6 single-dose ampules. Each 2.5 mL ampule contains 2.5 mg of dornase alfa (1 mg/mL): NDC 50242-100-40.

Storage and Handling

Store PULMOZYME ampules at a refrigerated temperature between 2°C to 8°C (36°F to 46°F) in their protective foil to protect from light and heat. Once the protective foil pouch is opened, the unused ampules must be kept refrigerated in the protective foil pouch to protect from light and heat. Do not use beyond the expiration date stamped on the ampule. During transport, keep the ampules refrigerated in their protective foil pouch to protect from light and heat. Do not use if the ampules are exposed to room temperature (22°C to 28°C [72°F to 82°F]) for more than a total of 60 hours. Avoid excessive heat and light.

17 PATIENT COUNSELING INFORMATION

Advise patients to read the FDA-approved patient labeling (Instructions for Use).

Preparation

Advise patients to squeeze each ampule prior to use in order to check for leaks. The solution should be discarded if it is cloudy or discolored. Once opened, the entire contents of the ampule must be used or discarded [see Dosage and Administration (2.2)].

Drug Incompatibilities

Instruct patients not to dilute or mix PULMOZYME with other drugs in the nebulizer. Mixing of PULMOZYME with other drugs could lead to adverse physicochemical and/or functional changes in PULMOZYME or the admixed compound [see Dosage and Administration (2.2)].

Storage

Instruct patients on the proper techniques to store and handle PULMOZYME [see How Supplied/Storage and Handling (16)].

Manufacturer's Instruction Manual

Instruct patients to read and follow the manufacturer's instruction manual for the proper use and maintenance of the jet nebulizer/compressor system, or the vibrating mesh nebulizer used in PULMOZYME delivery.

Pulmozyme® (dornase alfa)
Inhalation Solution

Manufactured by:
Genentech, Inc.
A Member of the Roche Group
1 DNA Way
South San Francisco, CA 94080-4990

US License No. 1048

©2024 Genentech, Inc. All rights reserved

©2024 Genentech, Inc.
Pulmozyme® is a registered trademark of Genentech, Inc.

INSTRUCTIONS FOR USE

PULMOZYME® (PULL-muh-zyme)

(dornase alfa)

Inhalation Solution

This Instructions for Use contains information on how to use PULMOZYME with Jet Nebulizers and Compressors

See the other side of this Instructions for Use for information on use of Pulmozyme with the recommended vibrating mesh nebulizers

Read and understand this Instructions for Use and the nebulizer manufacturer's instruction manual before you start taking Pulmozyme and each time you get a refill. There may be new information. This information does not take the place of talking to your doctor about your medical condition or your treatment.

A nebulizer and a compressor are used together to give a dose of Pulmozyme. A nebulizer changes the Pulmozyme liquid medicine into a fine mist you inhale by breathing through a mouthpiece. A compressor gives the nebulizer power and makes the nebulizer work.

Pulmozyme should only be used with the approved nebulizers and appropriate compressors as recommended below, or with the recommended vibrating mesh nebulizers (see other side of this Instructions for Use). Read and follow the manufacturer's instruction manual.

Do not use any other inhaled medicines in the nebulizer at the same time. Keep all other inhaled medicine systems completely separate from Pulmozyme.

Use the mouthpiece or face mask provided with the nebulizer kit.

If your child cannot breathe in or breathe out by mouth, you may use the PARI BABY reusable nebulizer, but you should discuss it with your doctor first. The PARI BABY nebulizer is the same as the PARI LC Plus Jet system, except the mouthpiece is replaced by a tight-fitting face mask connected to an elbow piece.

Follow the steps on this side of the Instructions for Use to give Pulmozyme using the following jet nebulizer systems

Jet Nebulizer | Compressor
Hudson T Up-draft II | A compressor with the following specifications is recommended:; - Approximate air flow of 3.5 L/min to 12 L/min at approximately 20 psi to 45 psi pressure
Marquest Acorn II | A compressor with the following specifications is recommended:; - Approximate air flow of 3.5 L/min to 12 L/min at approximately 20 psi to 45 psi pressure
PARI LC Plus | A compressor with the following specifications is recommended:; - Approximate air flow of 3.5 L/min to 12 L/min at approximately 20 psi to 45 psi pressure
PARI BABY | A compressor with the following specifications is recommended:; - Approximate air flow of 3.5 L/min to 12 L/min at approximately 20 psi to 45 psi pressure
Durable Sidestream | A compressor with the following specifications is recommended:; - Approximate air flow of 3.5 L/min to 12 L/min at approximately 20 psi to 45 psi pressure

For additional information on an appropriate compressor to use with Pulmozyme, read the manufacturer's instruction manual for the recommended nebulizer.

Important Information You Need to Know Before Using PULMOZYME

Read and follow the nebulizer manufacturer's instruction manual for correct use and maintenance:

- to clean the nebulizer before first use and after each use as recommended.
- to disinfect the nebulizer parts by using the disinfecting method recommended.
- to replace nebulizer parts as recommended.

Supplies you will need to give a dose of Pulmozyme (See Figure A):

- 1 Pulmozyme ampule
- Compressor
- Nebulizer cup and cap (screw-on or snap-on)
- Plastic T (not needed for Sidestream nebulizer or PARI BABY)
- Flexible aerosol tube (not needed for Sidestream nebulizer or PARI BABY)
- Mouthpiece (clean) or PARI BABY facemask
- Long connecting tube
- Nose clip (optional, not needed for PARI BABY)

Preparing the jet nebulizer and compressor:
Step 1. Clean a flat table surface and wash your hands.

- Clean a flat table surface.
- Wash your hands well with soap and water before using the Pulmozyme ampule and nebulizer. This helps prevent infection (See Figure B).

Step 2. Gather the nebulizer and test the compressor.

- Place the nebulizer parts on a clean, flat table surface within reach.
- Test the compressor by turning it on and putting your finger in front of the "air out" or "air" port to feel air flowing. Turn off the compressor (See Figure C).

Step 3. Gather the Pulmozyme ampule and check the expiration date.

- Remove 1 foil pouch of Pulmozyme from the refrigerator. Open the foil pouch and remove 1 ampule of Pulmozyme. Put the remaining ampules back in the foil pouch and return them to the refrigerator.
- Check the expiration (exp.) date printed on the ampule (See Figure D).
- Do not use the Pulmozyme ampule if the expiration date has passed.

Step 4. Check the Pulmozyme ampule.

- Check the ampule for leaks by turning it upside down and gently squeezing (See Figure E).
  Do not use the ampule if it is leaking. Throw it away and get a new one.
- Check the Pulmozyme liquid in the ampule and make sure it is clear and free of particles.
- Do not use Pulmozyme if the liquid is cloudy or discolored. Take the Pulmozyme back to the pharmacy, hospital, or clinic that gave you the medicine.

Step 5. Attach the long connecting tube to the compressor.

- Attach the long connecting tube to the "air out" or "air" port on the compressor (See Figure F).

Step 6. Attach the mouthpiece.

- Skip to Step 7 if you use the Sidestream nebulizer or the PARI BABY nebulizer.
- Push the mouthpiece into the wider end of the plastic T. Attach the flexible aerosol tube to the other end of the T (See Figure G).

Step 7. Remove the cap from the cup.

- Unscrew or unsnap the cap from the nebulizer cup (See Figure H).

- Put the nebulizer cup on the table face up and place the cap upside down on a clean surface (See Figure I).

Step 8. Open the Pulmozyme ampule.

- Hold the tab at the bottom of the Pulmozyme ampule firmly. Twist off the top. Do not squeeze the body of the ampule (See Figure J).

Step 9. Pour the full Pulmozyme dose into the nebulizer cup.

- Turn the ampule upside down and squeeze gently to empty the medicine into the nebulizer cup. Keep squeezing until the ampule is empty. It is very important you squeeze all of the medicine out of the ampule (See Figure K).
- Screw or snap the cap onto the nebulizer cup (See Figure L).

Step 10. Connect the plastic T.

- Connect the plastic T to the nebulizer cap (See Figure M).

- If you are using the Sidestream nebulizer, attach the mouthpiece to the top of the nebulizer (See Figure N).

- If you are using the PARI BABY nebulizer, connect the elbow piece and mask to the nebulizer outlet (See Figure O).

Step 11. Attach the long connecting tube to the cup.

- Connect the open end of the long connecting tube to the port on the bottom of the nebulizer cup by pushing up firmly (See Figure P).

Step 12. Turn on the compressor.

- Turn on the compressor and check to see that mist is coming out of the nebulizer (See Figure Q).

Taking your dose of Pulmozyme with a nebulizer:

Step 13. Breathe through the mouthpiece.

- Skip to Step 14 if you are using the PARI BABY to give Pulmozyme to your child.
- Place the mouthpiece between your teeth and on top of your tongue (See Figure R).
- Breathe slowly in and out through your mouth. Do not block the airflow with your tongue.
- Do not breathe through your nose. If you have problems breathing only through your mouth, use a nose clip (See Figure S).
- Do not be concerned if liquid droplets form in the long connecting tube during treatment. When the nebulizer begins spitting, gently tap the nebulizer cup and continue breathing until the nebulizer cup is empty or stops making mist (See Figure T).
- If you need to stop treatment before you are finished, or you begin coughing, turn off the compressor and do not spill any of the medicine.
- To start treatment again, turn on the compressor and continue breathing slowly in and out through your mouth.
- The complete treatment usually takes from 10 to 15 minutes for most nebulizers.
- If you are using the Sidestream nebulizer, treatment usually takes from 2 to 6 minutes.

- It is important to inhale the full dose of Pulmozyme. If you find a leak or feel any moisture coming from the nebulizer during treatment, turn off the compressor and check to make sure the nebulizer cap is sealed correctly before continuing (See Figure U).

If you are using the PARI BABY nebulizer to give Pulmozyme to your child, follow the instructions below in Step 14. If not, go to Step 15
Step 14. Breathing through the facemask.

- During the treatment your child may sit, lie down or stand.
- Place the facemask gently but firmly over your child's nose and mouth (See Figure V).
- Make sure there are no air gaps between the mask and your child's face. This will help make sure that your child will get the full dose of Pulmozyme.
- It is important that you try to keep the body of the nebulizer upright during the entire treatment (See Figure V). The elbow piece will allow you to move the mask for a good fit while keeping the nebulizer body upright.

- When the nebulizer begins "spitting," gently tap the nebulizer cup and continue treatment until the nebulizer is empty or stops making a mist (See Figure W).
- If you need to stop the treatment or your child begins to cough during treatment, turn the compressor off. Do not spill any Pulmozyme.
- If you have not removed the mask and you want to begin the treatment again, turn on the compressor.
- If you have removed the mask, repeat the steps above to replace the mask on your child's face and restart the compressor.
- The complete treatment usually takes from 10 to 15 minutes.

It is important that your child inhale the full dose of Pulmozyme. If you find a leak or feel moisture coming from the nebulizer during the treatment, turn off the compressor and make sure the nebulizer cap is sealed correctly before starting the compressor again (See Figure X).

After your treatment with Pulmozyme:
Step 15. Prepare the nebulizer for cleaning and storage.

- Turn off the compressor and take apart the nebulizer system. Set aside the flexible aerosol tube and the long connecting tube.
  Note: The Sidestream nebulizer does not use a flexible aerosol tube.
- Throw away the Pulmozyme ampule in your household trash.
- Follow the manufacturer's recommendations for care of your nebulizer and compressor.

How should I store Pulmozyme?

- Store Pulmozyme ampules at a refrigerated temperature between 36°F to 46°F (2°C to 8°C) in their protective foil pouch to protect from light and heat until you are ready to use them. When the protective foil pouch is opened, the unused ampules must be kept refrigerated in the protective foil pouch to protect from light and heat.
- When traveling, Pulmozyme ampules should be kept refrigerated in their protective foil pouch to protect from light and heat.
- Protect Pulmozyme from excessive heat and light.
- Do not use Pulmozyme if the ampules have been exposed to room temperature 72°F to 82°F (22°C to 28°C) for more than a total of 60 hours or if the solution has turned cloudy or discolored.
- Do not use Pulmozyme past the expiration date printed on the ampule.

Genentech, Inc.
A Member of the Roche Group
1 DNA Way
South San Francisco, CA 94080-4990
US License No. 1048

This Instructions for Use has been approved by the U.S. Food and Drug Administration.

Revised: 02/2024

INSTRUCTIONS FOR USE

PULMOZYME® (PULL-muh-zyme)

(dornase alfa)

Inhalation Solution

This Instructions for Use contains information on how to use PULMOZYME with the following recommended vibrating mesh nebulizers:

Recommended Vibrating Mesh Nebulizers

eRapid® Nebulizer System

Innospire Go

Pulmogine Vibrating Mesh Nebulizer

AireHealth Nebulizer™

Intelligent Mesh Nebulizer

See the other side of this Instructions for Use for information on use with Jet Nebulizers and Compressors

Read and understand this Instructions for Use and the nebulizer manufacturer's instruction manual before you start taking Pulmozyme and each time you get a refill. There may be new information. This information does not take the place of talking to your healthcare provider about your medical condition or your treatment.

This information does not take the place of the manufacturer's instruction manual for the vibrating mesh nebulizer.

The vibrating mesh nebulizer changes the Pulmozyme liquid medicine into a fine mist you inhale by breathing through a mouthpiece.

Do not use any other inhaled medicines in the nebulizer at the same time. Keep all other inhaled medication systems completely separate from Pulmozyme.

The eRapid Nebulizer System should only be used by adults and children who can use a mouthpiece, and not by younger children who need a mask to take Pulmozyme.

Follow the instructions on this side of the Instructions for Use to give Pulmozyme using a vibrating mesh nebulizer.

Important Information You Need to Know Before Using PULMOZYME

Read and follow the nebulizer manufacturer's instruction manual for correct use and maintenance:

- to clean the nebulizer before first use and after each use as recommended
- to disinfect the nebulizer parts by using the disinfecting method recommended
- to replace nebulizer parts as recommended

Supplies you will need to give a dose of PULMOZYME:

- 1 Pulmozyme ampule (See Figure A)
- Vibrating mesh nebulizer and its parts
- Manufacturer's instruction manual for the vibrating mesh nebulizer
- Nose clip (optional) (See Figure B)

Pulmozyme ampule
Figure A

Figure B

Prepare the vibrating mesh nebulizer:
Step 1. Clean a flat table surface and wash your hands.

- Clean a flat table surface.
- Wash your hands well with soap and water before using the Pulmozyme ampule and nebulizer. This helps prevent infection (See Figure C).

Figure C

Step 2. Gather the nebulizer. Make sure you have all parts and make sure they are clean and not damaged. Prepare and test it as recommended in the manufacturer's instruction manual.

- Place the vibrating mesh nebulizer on a clean, flat table surface within reach. Make sure you have followed the manufacturer's instruction manual to make sure that the nebulizer is charged and ready for use.

Step 3. Gather the Pulmozyme ampule and check the expiration date.

- Remove 1 foil pouch of Pulmozyme from the refrigerator. Open the foil pouch and remove 1 ampule of Pulmozyme. Put the remaining ampules back in the foil pouch and return them to the refrigerator.
- Check the expiration (exp.) date printed on the ampule (See Figure D).
  Do not use the Pulmozyme ampule if the expiration date has passed.

Figure D

Step 4. Check the Pulmozyme ampule.

- Check the ampule for leaks by turning it upside down and gently squeezing (See Figure E).
  Do not use the ampule if it is leaking. Throw it away and get a new one.
- Check the Pulmozyme liquid in the ampule and make sure it is clear and free of particles.
  Do not use Pulmozyme if the liquid is cloudy or discolored. Take the Pulmozyme back to the pharmacy, hospital, or clinic that gave you the medicine.

Figure E

Step 5. Put the vibrating mesh nebulizer together.

- Put the nebulizer together according to the step-by-step manufacturer's instruction manual.

Step 6. Prepare to take the Pulmozyme treatment.

- Follow the manufacturer's instruction manual on how to add the Pulmozyme medicine to the nebulizer.
- Open the Pulmozyme ampule.
- Hold the tab at the bottom of the Pulmozyme ampule firmly. Twist off the top. Do not squeeze the body of the ampule (See Figure F).
- Turn the ampule upside down and squeeze gently to empty the medicine into the medicine cup. Keep squeezing until the ampule is empty. It is very important that you squeeze out all the medicine in the ampule.

Taking your dose of Pulmozyme with a nebulizer:

- Read the manufacturer's instruction manual on how to turn the nebulizer on and off and follow the steps for how to:
  - take your nebulized treatment,
  - breathe through the mouthpiece or facemask,
  - restart treatment if you need to stop before you are finished, and
  - confirm that your treatment is complete.

Figure F

Step 7. Breathing through the mouthpiece.

- Skip to Step 8 if you are using a facemask to take your dose of Pulmozyme.
- Place the mouthpiece between your teeth and on top of your tongue.
  - Breathe slowly in and out through your mouth when using a mouthpiece. Do not block medicine flow with your tongue.
  - Do not breathe through your nose when using a mouthpiece. If you have problems breathing only through your mouth, use a nose clip (See Figure B).

Step 8. Breathing through the facemask.

- Place the facemask gently but firmly over the nose and mouth.
- Make sure there are no air gaps between the mask and the face. This will help make sure that you will get the full dose of Pulmozyme.

After Your Treatment with Pulmozyme:
Step 9. Clean the nebulizer

- Throw away the empty Pulmozyme ampule in your household trash.
- Clean the nebulizer thoroughly after each use. Follow the manufacturer's instruction manual for cleaning the nebulizer.
- All nebulizer parts must be cleaned after each use and disinfected after each day of use as recommended in the manufacturer's instruction manual.
- Replace the handset as recommended in the manufacturer's instruction manual.

How should I store Pulmozyme?

- Store Pulmozyme ampules at a refrigerated temperature between 36°F to 46°F (2°C to 8°C) in their protective foil pouch to protect from light and heat until you are ready to use them. When the protective foil pouch is opened, the unused ampules must be kept refrigerated in the protective foil pouch to protect from light and heat.
- When traveling, Pulmozyme ampules should be kept refrigerated in their protective foil pouch to protect from light and heat.
- Protect Pulmozyme from excessive heat and light.
- Do not use Pulmozyme if the ampules have been exposed to room temperature at 72°F to 82°F (22°C to 28°C) for more than a total of 60 hours or if the solution has turned cloudy or discolored.
- Do not use Pulmozyme past the expiration date printed on the ampule.

Genentech, Inc.

A Member of the Roche Group
1 DNA Way
South San Francisco, CA 94080-4990
US License No. 1048

This Instructions for Use has been approved by the U.S. Food and Drug Administration.

Revised: 02/2024

Representative sample of labeling (see the HOW SUPPLIED section for complete listing):

PRINCIPAL DISPLAY PANEL - 2.5 mg/2.5 mL Ampule Pouch Carton

NDC 50242-100-40

DORNASE ALFA

PULMOZYME®

INHALATION SOLUTION

2.5 mg/2.5 mL
(1 mg/mL)

Each carton contains 5 foil pouches
containing 6 single-dose ampules.

KEEP REFRIGERATED

11013278

Genentech, Inc.
A Member of the Roche Group
1 DNA Way, South San Francisco, CA 94080-4990
US License No.: 1048